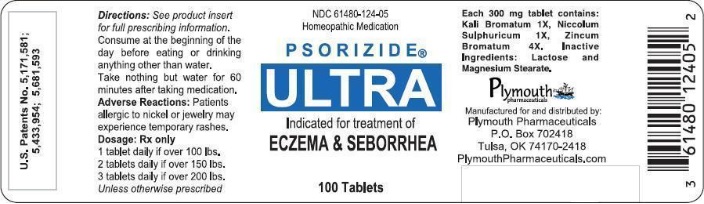 DRUG LABEL: Psorizide Ultra
NDC: 61480-124 | Form: TABLET
Manufacturer: PLYMOUTH HEALTHCARE PRODUCTS LLC
Category: homeopathic | Type: HUMAN PRESCRIPTION DRUG LABEL
Date: 20250107

ACTIVE INGREDIENTS: POTASSIUM BROMIDE 1 [hp_X]/1 1; NICKEL SULFATE 1 [hp_X]/1 1; ZINC BROMIDE 4 [hp_X]/1 1
INACTIVE INGREDIENTS: LACTOSE 264.27 mg/1 1; MAGNESIUM STEARATE 3 mg/1 1

PSORIZIDE®ULTRA

CAUTION:Federal law prohibits dispensing without a prescription.

DESCRIPTION

PSORIZIDE®ULTRA is a biochemical homeopathic medication indicated for the treatment of eczema and seborrhea.^24-26The active ingredients in each PSORIZIDE®ULTRA tablet consist of the following: Potassium Bromide (Kali Bromatum) 1X, Nickel Sulphate (Niccolum Sulphuricum) 1X and Zinc Bromide (Zincum Bromatum) 4x. These drug ingredients are listed in the Homoeopathic Pharmacopoeia of the United States (HPUS).^1

Inactive ingredients: Lactose and Magnesium Stearate.

Pharmacological class:Homeopathic drug

Dosage form:Oral 300 mg scored tablet. May be swallowed whole, chewed or dissolved in the mouth and swallowed.

CLINICAL PHARMACOLOGY

The active ingredients in PSORIZIDE®ULTRA are inorganic soluble mineral salts. The exact mechanism of action is unknown; however, it is believed PSORIZIDE®ULTRA addresses a primary genetic biochemical defect.

POTASSIUM BROMIDEdissolves and dissociates in the digestive tract into its ionic constituents. Each tablet contains approximately 15 mg bromide (calculated). Ionic bromide is rapidly and completely absorbed from the intestine and distributed almost exclusively in the extracellular fluids.^7,8Bromide is eliminated by the kidneys and the elimination half-life is 11-12 days. "Once a day" dosing will lead to a steady state concentration in about seven weeks.^7

NICKEL SULPHATEdissolves and dissociates in the digestive tract into its ionic constituents. Each tablet contains approximately 1.5 mg of ionic nickel (calculated). According to studies, 15% to 50% of ionic nickel is absorbed on a fasted stomach.^2Food markedly decreases the rate and extent of nickel absorption.^3,4Clinical studies show that serum concentrations of nickel are variable among patients after administering the same dosage.^5Peak serum nickel concentration is reached about two hours after oral administration. "Once a day" dosing leads to steady state serum concentrations in approximately one week. Nickel is in its highly stable divalent cation state and is therefore not expected to be metabolized to any significant degree in the body. Absorbed nickel is primarily excreted in the urine and elimination half-life is about 21 hours.^3,5Renal clearance is rapid and efficient, and nickel does not accumulate in the body.^6

CLINICAL STUDIES

A variety of controlled clinical studies have been performed using various sources of both nickel and bromide in over 300 subjects. Clinical efficacy and safety have been documented in a significant number of subjects. Published and unpublished reports are available upon request.^9,22,23

INDICATIONS

PSORIZIDE®ULTRA is indicated for the treatment of moderate to severe eczema, atopic dermatitis, seborrhea and seborrheic dermatitis. It has been found to work well with variety of combination therapies. Psoriasis also responds, but generally has a more favorable response to PSORIZIDE®Forte (NDC 61480-255-05.)

CONTRAINDICATIONS

Although there are no known contraindications, patients who are allergic to any PSORIZIDE®ULTRA ingredient should consult a physician prior to taking the medication. (Refer to Section on Hypersensitivity)

WARNING

Do not use if imprinted seal under bottle cap is missing or broken. Do not use if pregnant or nursing. If allergic to nickel or metal objects such as jewelry or if there is a history of blistering hand eczema, see PRECAUTIONSfor hypersensitivity information. Lactose intolerant patients may have gastrointestinal difficulty. This has very rarely been reported at the doses used.

PRECAUTIONS

Carefully adjust dosage to weight when treating young children. Do not use in cases of kidney disease. If skin rash appears or if nervous symptoms persist, recur frequently, or are unusual, discontinue use.

Hypersensitivity

Caution should be used when administering to patients with a history of contact sensitivity to nickel (common metal exposure) or if there is a history of vesicular hand eczema (dyshidrosis, pomphylox). Nickel allergy may be confirmed by a positive nickel patch test. Most patients with hand eczema, positive nickel allergy history, or a positive nickel patch test do nothave any untoward reaction to administration of PSORIZIDE®ULTRA. If there is a history of nickel sensitivity or dyshidrotic hand eczema, begin with a very low dose and slowly increase to a recommended starting dose over a period of 5 weeks as tolerated, thus allowing progressive GI absorption*.

*Nickel desensitization schedule:
Week | Amount of Time to Take Medication Prior to Breakfast
Week 1 | With Breakfast
Week 2 | 15 min
Week 3 | 30 min
Week 4 | 45 min
Week 5 and thereon | 1 hour

If new pruritic rashes occur or persist, discontinue PSORIZIDE®ULTRA and treat appropriately. Do not use if there is a history of extra-cutaneous hypersensitivity to nickel or bromide.

Information for patients

Patients using PSORIZIDE®ULTRA should receive the following information and instructions:

1. This medication is to be used as directed by a physician.
2. It is important to take orally at the beginning of the day on an empty stomach (or any convenient time after having taken nothing but water for at least 7 hours) and to eat or drink nothing but water for at least one hour afterwards to avoid interference with absorption.

Drug interactions

There are no known drug interactions.

Carcinogenesis, mutagenesis, impairment of fertility

No studies have been done on the carcinogenesis or mutagenesis, or impairment of fertility of PSORIZIDE®ULTRA. No carcinogenesis or mutagenesis has been reported in multiple animal studies for oral administration of soluble nickel and bromide salts (active ingredients) even at very high doses.^10-16

Effects of soluble potassium bromide

KBr is not listed as a carcinogen by the NTP, IARC, and OSHA.^18

Effects of soluble nickel sulphate

Studies on experimental animals have never indicated that nickel, at any dose, is a carcinogen when introduced to the body orally. Furthermore, Nickel sulphate and other highly water soluble nickel salts, have never been known to induce carcinogenesis via any route of introduction including: oral, inhalation, cutaneous, IM, or IP.^10-12,17No adverse effects were noted on fertility or reproduction in a 3-generational study of albino Wistar rats fed up to 1000 ppm Ni per day, which is equivalent to 50 mg/kg body weight per day Ni.^17

Pregnancy

Pregnancy category C

Animal reproduction studies have not been conducted with PSORIZIDE®ULTRA. PSORIZIDE®ULTRA should not be given to a pregnant woman.

Nursing mothers

It is not known whether this drug is excreted in human milk. However, since many drugs are excreted in human milk, caution should be exercised when PSORIZIDE®ULTRA is administered to a nursing woman.

Pediatric use

Carefully adjust dosage to weight when treating young children.

ADVERSE REACTIONS

PSORIZIDE®ULTRA contains low doses of active ingredients. Therefore there are minimal known side effects.
(see PRECAUTIONSfor hypersensitivity information)

OVERDOSAGE

Potassium bromide toxicity

Indications of toxicity due to oral overdosage of bromide may include nausea, vomiting, apathy, disturbed coordination, loss of memory, drowsiness, loss of emotional control, agitation, hallucination, tremors, depressed reflexes, stupor, and coma. Acute toxic reactions in humans have been reported at doses as low as 1000 mg.^21This level is 67 times the dose received in one tablet of PSORIZIDE®ULTRA.

Nickel sulphate toxicity

The oral rat LD50for nickel sulphate hexahydrate is 275 mg/kg.^19Symptoms of toxicity due to oral overdosage of nickel sulphate may include nausea, vomiting, abdominal discomfort, diarrhea, giddiness, lassitude, headaches, cough, and shortness of breath.^20The lowest observed transitory toxic effects from human ingestion of soluble nickel salts is approximately 8 mg nickel/kg body weight.^20This is 80 times the maximum dose recommended for PSORIZIDE®ULTRA. (See below).

DOSAGE AND ADMINISTRATION

Absorption of nickel sulphate is variable among individuals. For maximum absorption, tablets should be taken orally at the beginning of the day (or any convenient time after having taken nothing but water for at least 7 hours). Take nothing but water for one hour after taking medication to aid absorption.

Weight | Starting Dose | Max. Dose
50-100 lbs | ½ tablet | 1 tablet
100-150 lbs | 1 tablet | 2 tablets
150-200 lbs | 2 tablets | 4 tablets
over 200 lbs | 3 tablets | 6 tablets

In the setting of renal impairment, dosage should be adjusted and serum nickel and bromide levels should be followed.Steady state trough level should be drawn priorto ingesting the day's dose after one week of dosing or at appropriate intervals. Target trough serum nickel level is 20-40 mcg/L. (Warning: post dose peak levels are unreliable.) Treatment duration depends on the individual. Increase dose as needed on a monthly basis.

Maintenance phase

In order to maintain symptomatic relief, medication may be continued at the same or reduced initial phase dose level.

INACTIVE INGREDIENTS

Lactose and magnesium stearate.

HOW SUPPLIED

Scored tablets, off white in color with green speckles, with LL and scoreimprinted on same side, in child-resistant and tamper-resistant bottles of 100. NDC 61480-124-05.

REFERENCES

1. The Homeopathic Pharmacopoeia of the United States (HPUS), 8thEdition, Falls Church, Virginia, 1979.
2. Sunderman FW jr., Biological monitoring of nickel in humans. Scand J Work Environ Health 1993; 19 suppl 1:34-38.
3. Sunderman FW jr., Hopfer SM, Sweeny KR, Marcus AH, Most BM, Creason J. Nickel absorption and kinetics in human volunteers, P.S.E.B.M. 1989; 191:5-11.
4. Solomons NW, Viteri F, Shuler TR, Nielsen FH. Bioavailability of nickel in man: Effects of foods and chemically-defined dietary constituents on the absorption of inorganic nickel. J Nutr 1982; (2); 112; 39-50.
5. Christensen OB, Iagesson V. Nickel concentration of blood and urine after oral administration. Annals of Clinical and Laboratory Science 1981;2(2);119-125.
6. Nielsen FH. Is nickel nutritionally important? Nutrition Today 1993;28(1):14-19.
7. Vaiseman N, Koren G, Pencharz P. Pharmacokinetics or oral and intravenous bromide in normal volunteers. Clinical Toxicology 1986;24(5):403-413.
8. Van Leeuwen FXR, Sangster B. The toxicology of bromide ion. CRC Critical Reviews in Toxicilogy 1987; 18(3):189-213.
9. Smith SA. Oral supplementation of nickel and bromide in psoriasis vulgaris using nickel sulfate and sodium bromide. 1995 (unpublished report).
10. Miller MJ, Bogdan KG, Leach JF, and Gray AJ. Ambient air criteria document, Bureau of Toxic Substance Assessment, New York Department of Health, Albany, NY 1989.
11. US EPA, Environmental Criteria and Assessment Office, Office of Health and Environmental Assessment, health assessment document for nickel and nickel compounds. Washington DC, EPA/600/8-83/012FF.
12. US EPA, Environmental Criteria and Assessment Office, Office of health and Environmental Assessment. Drinking water quantification of toxicological effects for nickel. ECAO-CIN-443.1991
13. US FDA, Center for Food Safety and Applied Nutrition. Guidance document for nickel in shellfish. 1993.
14. Buselmaier W. von, Rohrborn G, and Propping G. Mutagenitats – Untersuchugen mit Pestiziden im Host – Mediated Assay und mit dem Dominanten Letaltest an der Maus. Biol Zbl 1972; 91:311-325.
15. IARC Monograph on the Evaluation of Carcinogenic Risk of Chemicals to Man. IRC Publication #11, Lyon, France 1976.
16. Corbett TH, Heidelberger C, and Dove WF. Determination of mutagenic activity to bacteriiophage T4 or carcinogenic and non-carcinogenic compounds. Mol Pharmacol 1970;6:667-669.
17. Ambrose AM, Larson PS, Borselleca JF, and Hennigar GR, Jr. Long term toxicologic assessment of nickel in rats and dogs. Journal of Food Science and Technology 1976;13:181-187.
18. MSDS Sheet No. 247 Potassium Bromide. Schenectady, NY: Genium Publishing Corp 1991.
19. MSDS Sheet No. 37 Nickel Sulfate. Schenectady, NY: Genium Publishing Corp 1993.
20. Sunderman FW Jr., Dingle B, Hopfer SM, and Swift T. Acute nickel toxicity in electroplating workers who accidentally ingested a solution of nickel sulfate and nickel chloride. American Journal of Industrial Medicine 1988;14;257-266.
21. Martindale: The Extra Pharmacopoeia 27thed. Wade A, editor. The Pharmaceutical Press: London, 1977, pp273-274.
22. Smith SA, et al, Improvement of Psoriasis Vulgaris with Oral Nickel Dibromide. Archives of Dermatology 1997; 133:661-663.
23. Smith SA, Baker AE, etal. Effective Treatment of Seborrheic Dermatitis Using a Low Dose, Oral Homeopathic Medication... Alt Med Rev 2002; 7, pp59-67
24. Reckeweg, Hans-Heinrich, Materia Medica, 1983, first English edition.
25. Boericke, William, Materia Medica with Reperatory, 1927, ninth edition.
26. Clarke, John Henry, A Dictionary of Practical Materia Medica, 1921, reprint edition 1996.

Plymouth Pharmaceuticals Inc. dba LOMA LUX Laboratories; P.O. BOX 702418; Tulsa, OK 74170-2418

Phone 800.316.9636, 918.664.9882, Fax 918.664.9884

Revised 9.27.05 mn

PRINCIPAL DISPLAY PANEL - 100 Tablet Bottle

NDC 61480-124-05

Homeopathic Medication

PSORIZIDE®
ULTRA

Indicated for treatment of
ECZEMA & SEBORRHEA

100 Tablets